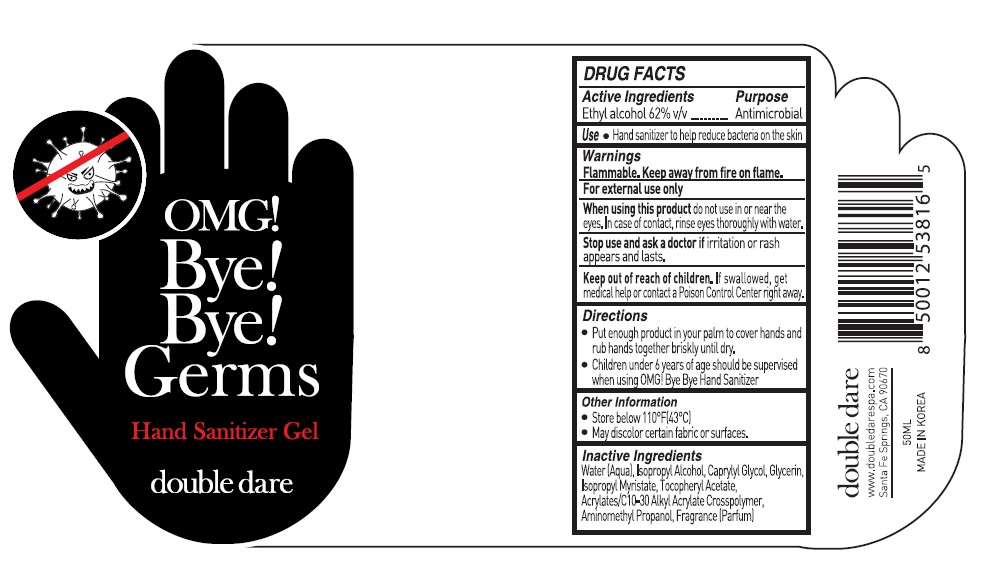 DRUG LABEL: Bye Bye Germs OMG Hand Sanitizer Gel
NDC: 73724-001 | Form: GEL
Manufacturer: JK BEAUTY GROUP, INC.
Category: otc | Type: HUMAN OTC DRUG LABEL
Date: 20200424

ACTIVE INGREDIENTS: ALCOHOL 0.62 mg/1 mL
INACTIVE INGREDIENTS: WATER; ISOPROPYL ALCOHOL; CAPRYLYL GLYCOL; GLYCERIN; ISOPROPYL MYRISTATE; .ALPHA.-TOCOPHEROL ACETATE, D-; CARBOMER INTERPOLYMER TYPE A (ALLYL SUCROSE CROSSLINKED); AMINOMETHYLPROPANOL

Bye! Bye! Germs OMG! Hand Sanitizer Gel

Active ingredient

Ethyl alcohol 62% v/v

Purpose

Antimicrobial

Use

- Hand sanitizer to help reduce bacteria on the skin

Warnings

Flammable. Keep away from fire or flame.

For external use only

When using this product do not use in or near the eyes. In case of contact, rinse eyes thoroughly with water.

Stop use and ask a doctor if irritation or rash appears and lasts

Keep out of reach of children. If swallowed, get medical help or contact a Poison Control Center right away.

Directions

- Put nough produt in your palm to cover hands and rub hands together briskly until dry.
- Children under 6 years of age should be supervised when using PURELL

Other information

- Store below 110°F (43°C)
- May discolor certain fabrics or surfaces

Inactive ingredients

Water (Aqua), Isopropyl Alcohol, Caprylyl glycol, Glycerin, Isopropyl Myristate, Tocopheryl Acetate, Acrylates/C10-30 Alkyl Acrylate Crosspolymer, Aminomethyl Propanol, Fragrance (Parfum)